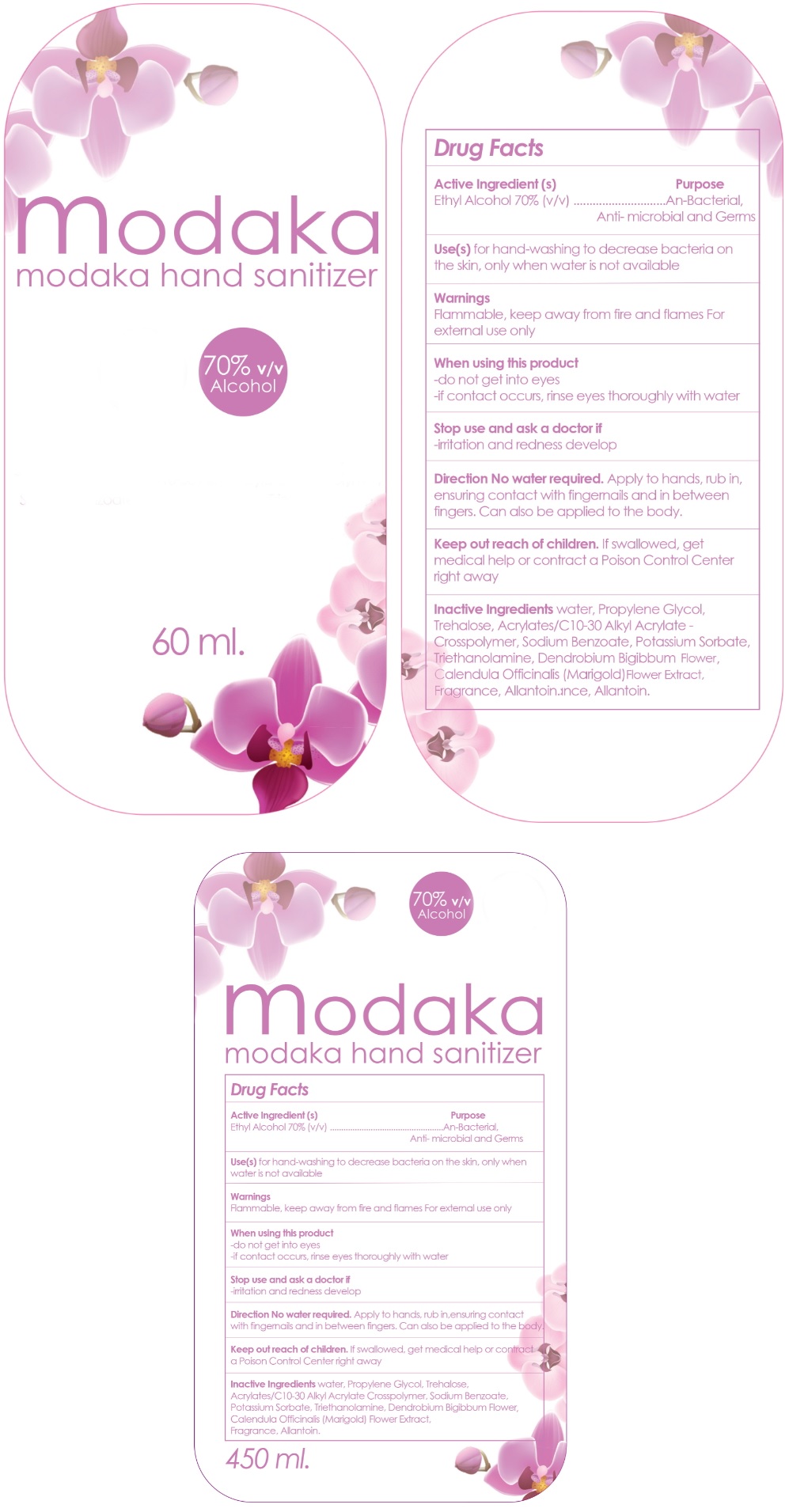 DRUG LABEL: MODAKA
NDC: 77779-002 | Form: GEL
Manufacturer: WE LABS COMPANY LIMITED
Category: otc | Type: HUMAN OTC DRUG LABEL
Date: 20200515

ACTIVE INGREDIENTS: ALCOHOL 750 mg/1 mL
INACTIVE INGREDIENTS: WATER; PROPYLENE GLYCOL; TREHALOSE; CARBOMER INTERPOLYMER TYPE A (ALLYL SUCROSE CROSSLINKED); SODIUM BENZOATE; POTASSIUM SORBATE; TROLAMINE; DENDROBIUM BIGIBBUM FLOWER; CALENDULA OFFICINALIS FLOWER; ALLANTOIN

modaka Hand Sanitizer

Active Ingredient (s)

Ethyl Alcohol 70% v/v

Purpose

Anti-Bacterial, Anti-microbial and Germs

INDICATIONS AND USAGE

Use (s) for hand-washing to decrease bacteria on the skin, only when water is not available

Warnings

Flammable, keep away from fire and flames

For external use only

When using this product

- do not get into eyes

- if contact occurs, rinse eyes thoroughly with water

Stop use and ask a doctor if

- irritation and redness develop

KEEP OUT OF REACH OF CHILDREN

Keep out reach of children. If swallowed, get medical help or contact a Poison Control Center right away

DOSAGE AND ADMINISTRATION

Direction No water required. Apply to hands, rub in, ensuring contact with fingernails and in between fingers. Can also be applied to the body.

INACTIVE INGREDIENT

Inactive Ingredients water, Propylene Glycol, Trehalose, Acrylates/C10-30 Alkyl Acrylate Crosspolymer, Sodium Benzoate, Potasssium Sorbate, Triethanolamine, Dendrobium Bigibbum Flower, Calendula Officinalis (Marigold) Flower Extract, Fragrance, Allantoin.